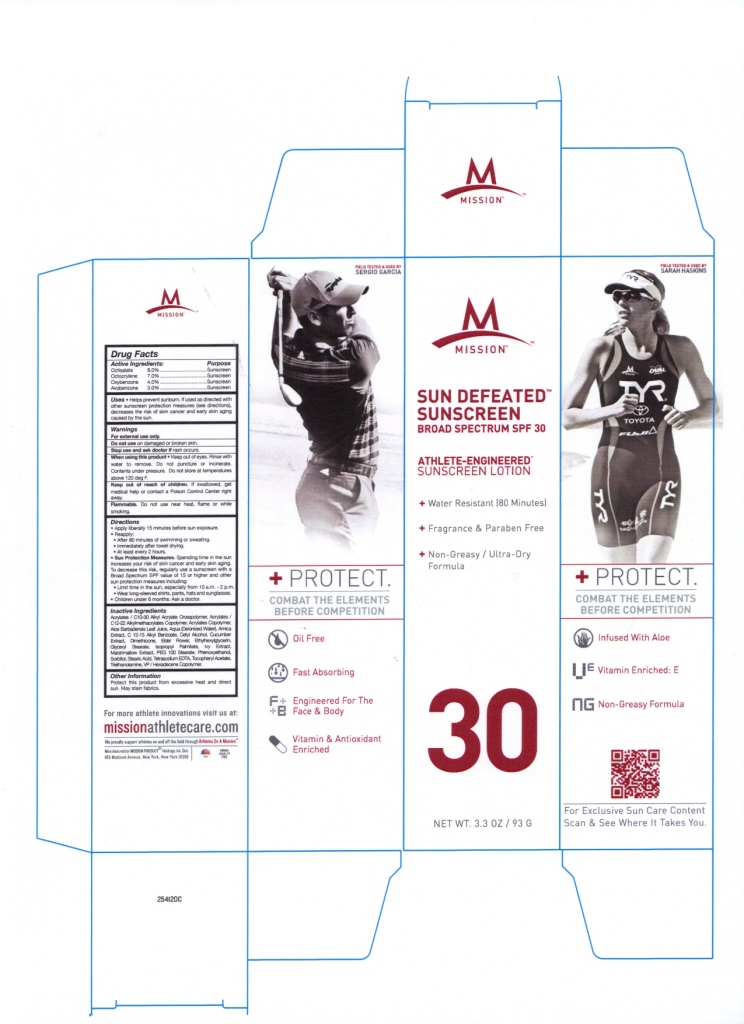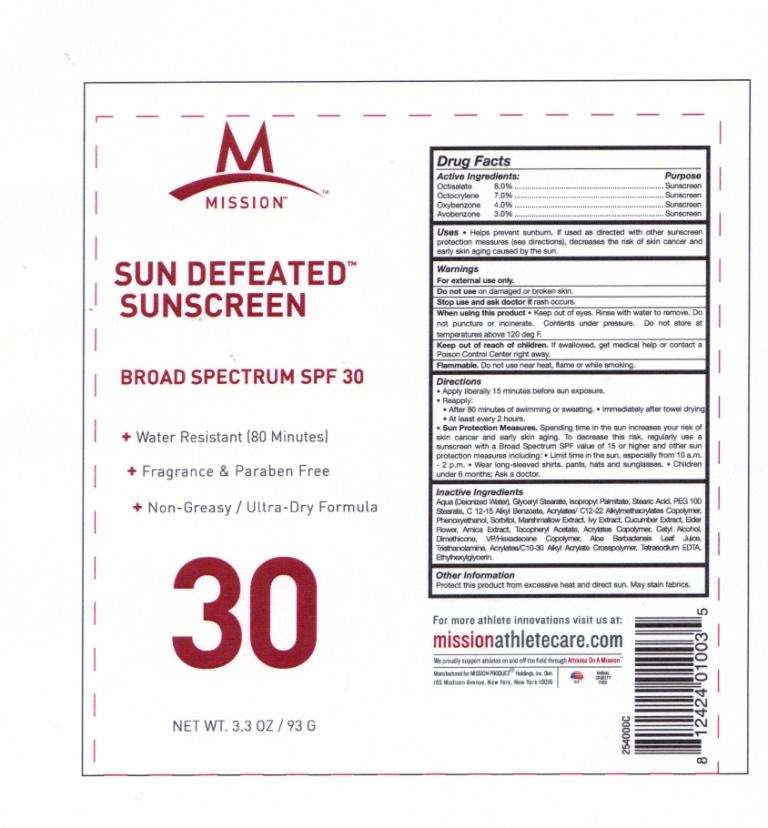 DRUG LABEL: Sun Defeated Sunscreen
NDC: 51702-114 | Form: LOTION
Manufacturer: Mission
Category: otc | Type: HUMAN OTC DRUG LABEL
Date: 20120312

ACTIVE INGREDIENTS: Avobenzone 2.79 g/93 g; Octocrylene 6.51 g/93 g; Oxybenzone 3.74 g/93 g; Octisalate 7.44 g/93 g
INACTIVE INGREDIENTS: WATER; GLYCERYL MONOSTEARATE; ISOPROPYL PALMITATE; STEARIC ACID; PEG-100 STEARATE; ALKYL (C12-15) BENZOATE; SORBITOL; ALTHAEA OFFICINALIS ROOT; HEDERA HELIX LEAF; CUCUMBER JUICE; SAMBUCUS NIGRA FLOWER; ARNICA MONTANA; .ALPHA.-TOCOPHEROL ACETATE, D-; CARBOMER COPOLYMER TYPE A; CETYL ALCOHOL; DIMETHICONE; ALOE VERA LEAF; TROLAMINE; EDETIC ACID; PHENOXYETHANOL; ETHYLHEXYLGLYCERIN

Drug Facts

Active Ingredients: Purpose:

Avobenzone (3.0%)..............................................................Sunscreen

Octocrylene (7.0%)...............................................................Sunscreen

Oxybenzone (4.0%)...............................................................Sunscreen

Octisalate (8.0%)...................................................................Sunscreen

PURPOSE

- Medium UVB sunburn/UVA protection
- For skin highly sensitive to sunburn
- Retains SPF after 80 minutes of activity

Warnings: FOR EXTERNAL USE ONLY

UV exposure from the sun increases the risk of skin cancer, premature skin aging, and other skin damage. It is important to decrease UV exposure by limiting time in the sun, wearing protective clothing, and using sunscreen.

- When using this product keep out of eyes. Rinse with water to remove. Do not puncture or incinerate. Contents under pressure. Do not store at temperatures above 120 deg F.
- Stop use and ask a doctor if skin rash occurs.
- Keep out of reach of children. If swallowed, get medical help or contact a Poison Control Center right away.

DOSAGE AND ADMINISTRATION

Directions: Apply liberally before sun exposure. Apply and reapply, as directed to avoid lowering protection. Reapply after 80 minutes of swimming or sweating and after towel drying. Otherwise reapply at least every two hours. Children under 6 months: ask a doctor.

INACTIVE INGREDIENT

Aqua (Deionized Water), Glyceryl Stearate, Isopropyl Palmitate, Stearic Acid, PEG 100 Stearate, C 12-15 Alkyl Benzoate, Acrylates/C12-22 Alkylmethacrylates Copolymer, Sorbitol, Marshmallow Extract, Ivy Extract, Cucumber Extract, Elder Flower, Arnica Extract, Tocopheryl Acetate, Acrylates Copolymer, Cetyl Alcohol, Dimethicone, VP/Hexadecene Copolymer, Aloe Barbadenis Leaf Juice, Triethanolamine, Acrylates/C10-30 Alkyl Acrylate Crosspolymer, EDTA, Phenoxyethanol, Ethylhexylglycerin